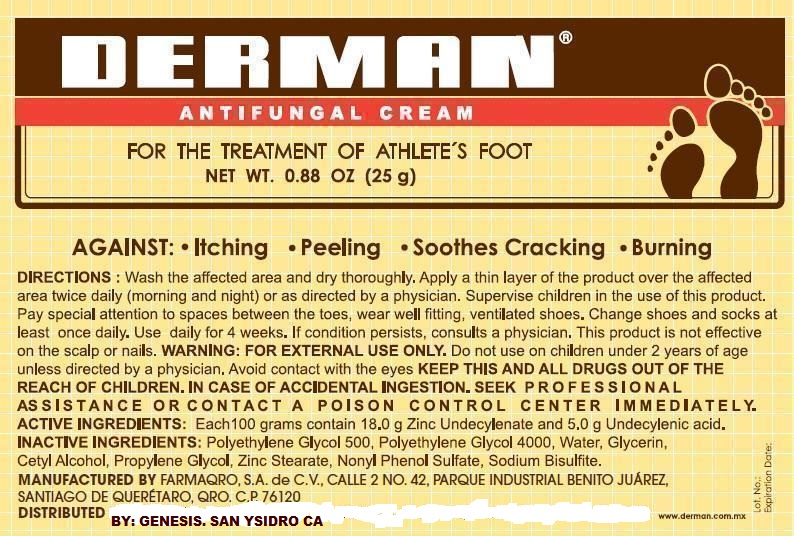 DRUG LABEL: DERMAN ANTIFUNGAL
NDC: 69772-125 | Form: CREAM
Manufacturer: Teresa Cecena DBA Genesis
Category: otc | Type: HUMAN OTC DRUG LABEL
Date: 20150520

ACTIVE INGREDIENTS: UNDECYLENIC ACID 5 g/100 g; ZINC UNDECYLENATE 18 g/100 g
INACTIVE INGREDIENTS: METHYLPARABEN; POLYETHYLENE GLYCOL 500; POLYETHYLENE GLYCOL 4000; GLYCERIN; CETYL ALCOHOL; PROPYLENE GLYCOL; WATER; ZINC STEARATE; SODIUM BISULFITE

ACTIVE INGREDIENTS.

Zinc undercylenate 18%

undecylenic acid 5%

PURPOSE

Antifungal

USES

For the treatment of athlete's foot. Relieves itching-scaling-cracking-buring.

WARNINGS

AVOID CONTACT WITH EYES

Keep this and all drugs out od the reach of children. In case of accidental ingestion. seel professional assistance or contact a poison control center immediately.

Do not use in pregnancy and children under 2 years of age unless directed by a physician.

For external use only

In case of accidental ingestion seek professional assistance or contac a poison control center immediately.

DOSAGE AND ADMINISTRATION

Wash the affected area and dry throughly. Appy a thin layer of the product over the affected area ttwice daily (morning and night) or as directed by a physician. Supervise children in the use of this product Pay special attention to space between the toes, wear well fitting, ventilated shoes. Change shoes and socks at least once daily. Use daily for 4 weeks. If condition persists, consults a physician.

This product is not effective on the scalp or nails.

INACTIVE INGREDIENT

Polyethylene Glyctol 500, polythylene glycol 4000, water, glycerin, cetyl alcohol, propylene, gycol, zinc stearate, nonyl phenol sulfate, sodium bisulfite.

KEEP OUT OF REACH OF CHILDREN

KEEP THIS AND ALL DRUGS OUT OF REACH OF CHILDREN

INDICATIONS AND USAGE

Wash the affected area and dry throughly. Appy a thin layer of the product over the affected area ttwice daily (morning and night) or as directed by a physician. Supervise children in the use of this product Pay special attention to space between the toes, wear well fitting, ventilated shoes. Change shoes and socks at least once daily. Use daily for 4 weeks. If condition persists, consults a physician.

This product is not effective on the scalp or nails